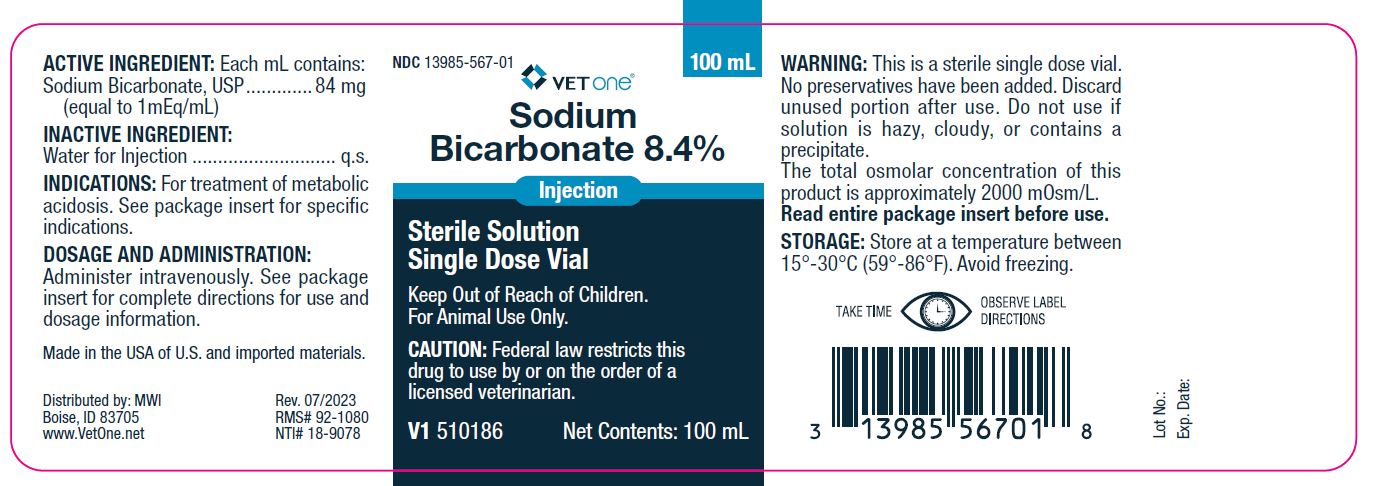 DRUG LABEL: Sodium Bicarbonate
NDC: 13985-567 | Form: INJECTION
Manufacturer: MWI (VetOne)
Category: animal | Type: PRESCRIPTION ANIMAL DRUG LABEL
Date: 20240513

ACTIVE INGREDIENTS: SODIUM BICARBONATE 84 mg/1 mL
INACTIVE INGREDIENTS: WATER

MWI (VetOne)
Sodium Bicarbonate 8.4%

INDICATIONS:

For treatment of metabolic acidosis. See package insert for specific indications.

Active Ingredient: Each mL contains:

Sodium Bicarbonate..........................84 mg

(equal to 1 mEq/mL)

Inactive Ingredient:

Water for Injection...........................q.s.

Dosage and Administration:

Administer intravenously. See package insert for complete directions for use and dosage information.

Take Time Observe Label Directions

NDC 13985-567-01

100 mL

VetOne®

Sodium Bicarbonate 8.4%

Injection

Sterile Solution

Single Dose Vial

V1 510186

Net Contents: 100 mL

Made In USA of U.S. and imported materials.

Distributed by:MWI

Boise, ID 83705

www.VetOne.net

Storage:

Store at a temperature between 15°-30°C (59°-86°F). Avoid freezing.

Keep out of reach of children.

For veterinary use only.

Caution: Federal law restricts this drug to use by or on the order of a licensed veterinarian.

Warning:

This is a sterile single dose vial. No preservatives have been added. Discard unused portion after use. Do not use if solution is hazy, cloudy, or contains a precipitate. The total osmolar concentration of this product is approximately 2000 mOsm/L.

Read entire package insert before use.

Package Insert

VetOne®

SODIUM BICARBONATE 8.4%

Injection

STERILE NONPYROGENIC SOLUTION

FOR VETERINARY USE ONLY

DESCRIPTION: Sodium Bicarbonate 8.4% is a sterile
nonpyrogenic preparation of sodium bicarbonate
(NaHCO3) in Water for Injection. Each 100 mL contains
8.4 grams of sodium bicarbonate (100 mEq/100 mL
each of sodium and bicarbonate). This concentrated
solution has an approximate pH of 7.8.

ACTIONS: Sodium Bicarbonate is useful in the
treatment of metabolic acidosis due to a wide variety of
causes. Sodium Bicarbonate therapy increases plasma
bicarbonate, buffers excess hydrogen ion concentration,
raises blood pH and reverses the clinical manifestations
of acidosis. Sodium Bicarbonate also alkalinizes the
urine.

INDICATIONS: Sodium Bicarbonate is indicated in the
treatment of metabolic acidosis which may be due to
severe renal disease, uncontrolled diabetes, circulatory
insufficiency due to shock or severe dehydration,
cardiac arrest and severe primary lactic acidosis.
Sodium Bicarbonate is also indicated in severe diarrhea
which is often accompanied by a significant loss of
bicarbonate. Sodium Bicarbonate 8.4% is indicated in
the treatment of metabolic acidosis in cattle, horses,
sheep, swine and dogs depending upon causative
factor.

CONTRAINDICATIONS: Sodium Bicarbonate is contraindicated
in animals losing chloride by vomiting and in
animals receiving diuretics known to produce a
hypochloremic alkalosis.

PRECAUTIONS: Bicarbonate therapy is directed at
producing a substantial correction of low total CO2
content and blood pH, but risks of overdosage and
alkalosis should be avoided. Repeated fractional doses
and periodic monitoring by appropriate laboratory tests
are therefore recommended to minimize the possibility
of overdosage. Sodium Bicarbonate addition to
parenteral solutions containing calcium should be
avoided except where compatibility has been previously
established. Precipitation or haze may result from
sodium bicarbonate-calcium admixtures, and the
resulting solution should not be administered.

DOSAGE AND ADMINISTRATION: Sodium Bicarbonate
8.4% is injected intravenously. Caution should be taken
in emergencies where very rapid infusion of large
quantities of bicarbonate is indicated, such as cardiac
arrest. Sodium Bicarbonate solutions are hypertonic
and may produce an undesirable rise in plasma sodium
concentration during the process of correction of
metabolic acidosis. During cardiac arrest, however, the
risks from acidosis exceed those of hypernatremia. In
cattle and horses, 200 to 300 mL of 8.4% solution may
be given undiluted by rapid infusion using a needle and
syringe.

Sodium Bicarbonate 8.4% solution is often added to other
intravenous fluids for the less urgent forms of metabolic
acidosis. The amount of bicarbonate to be given over a
4 to 8 hour period is approximately 2 to 5 mEq per kg of
body weight (1-2.5 mL/lb body weight) depending upon
the severity of the acidosis as judged by the lowering of
total CO2 content, blood pH and clinical condition of the
animal.

Bicarbonate therapy should always be planned in
stepwise fashion since the degree of response from a
given dose is not precisely predictable. Initially, an
infusion of 2 to 5 mEq per kg of body weight over a
period of 4 to 8 hours will produce a measurable
improvement in the abnormal acid-base status of the
blood. Completion of therapy is dependent upon the
clinical response of the animal. If severe symptoms
have abated, then frequency of administration and size
of the dose should be reduced.

OVERDOSAGES: In case alkalosis occurs, the
bicarbonate should be stopped and the animal
managed according to the degree of alkalosis present.
Sodium chloride injection (0.9%) may be given intravenously;
potassium chloride also may be indicated if
there is hypokalemia. Severe alkalosis may be accompanied
by hyperirritability or tetany, and these
symptoms may be controlled by calcium gluconate. An
acidifying agent such as ammonium chloride may also
be indicated in severe alkalosis.

HOW SUPPLIED: Sodium Bicarbonate 8.4% is
supplied in a 100 mL single dose vial.

WARNING: This is a sterile single dose vial. No preservatives
have been added. Discard unused portion after
use. Do not use if solution is hazy, cloudy or contains a
precipitate.

Store at a temperature between 15°-30° C (59°-86° F).

CAUTION: Federal law (U.S.A.) restricts this drug to
use by or on the order of a licensed veterinarian.

Questions? Call 859-254-1221 or toll-free 800-621-8829.

Distributed by: MWI

Boise, ID 83705

www.VetOne.net

VetOne®